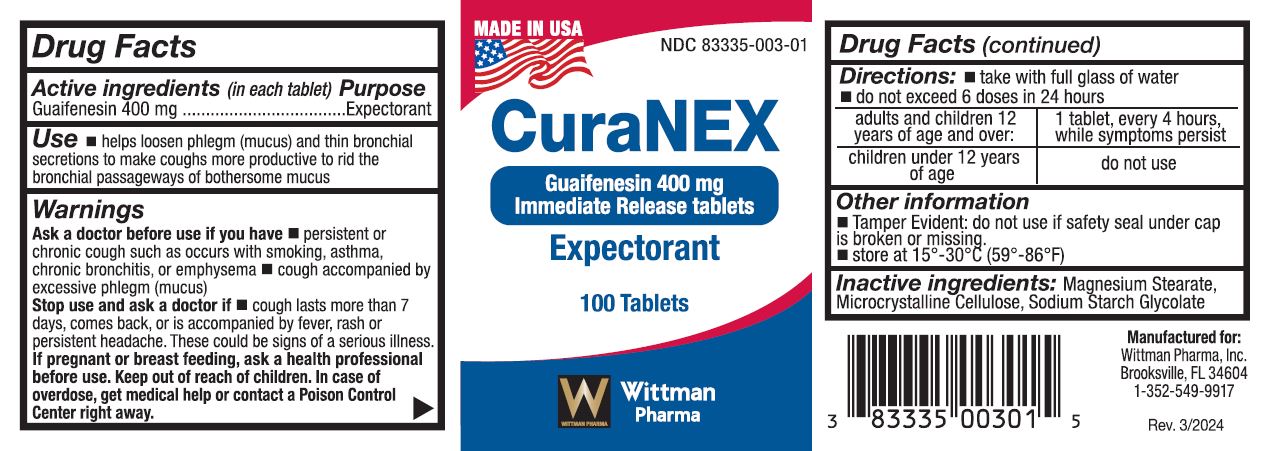 DRUG LABEL: CurNEX
NDC: 83335-003 | Form: TABLET
Manufacturer: Wittman Pharma, Inc.
Category: otc | Type: HUMAN OTC DRUG LABEL
Date: 20240308

ACTIVE INGREDIENTS: GUAIFENESIN 400 mg/1 1
INACTIVE INGREDIENTS: MAGNESIUM STEARATE; MICROCRYSTALLINE CELLULOSE; SODIUM STARCH GLYCOLATE TYPE A

CuraNEX

Directions

- take with full glass of water
- do not exceed 6 doses in 24 hours

- Adults and children 12 years of age and over; take 1 tablet every 4 hours while symptoms persist
- Children under 12 years of age; do not use

Warnings

Ask a doctor before use if you have * persistent or chronic cough such as occurs with smoking, asthma, chronic bronchitis, or emphysema * cough accompanied by excessive phlegm (mucus)

Stop use and ask a doctor if * cough lasts more than 7 days, comes back, or is accompanied by fever, rash or persistent headache. These could be signs of a serious illness.

If pregnant or breast feeding, ask a health professional before use. Keep out of reach of children. In case of overdose, get medical help or contact a Poison Control Center right away.

INACTIVE INGREDIENT

Inactive Ingredients: Magnesium Stearate, Microcrystalline Cellulose, Sodium Starch Glycolate

INDICATIONS AND USAGE

- helps loosen phlegm (mucus) and thin bronchial secretions to make coughs more productive to rid the bronchial passageways of bothersome mucus

Keep out of reach of children. In case of overdose, get

medical help or contact a Poison Control Center right away.

Purpose: Expectorant

ACTIVE INGREDIENT

Guaifenesin 400 mg